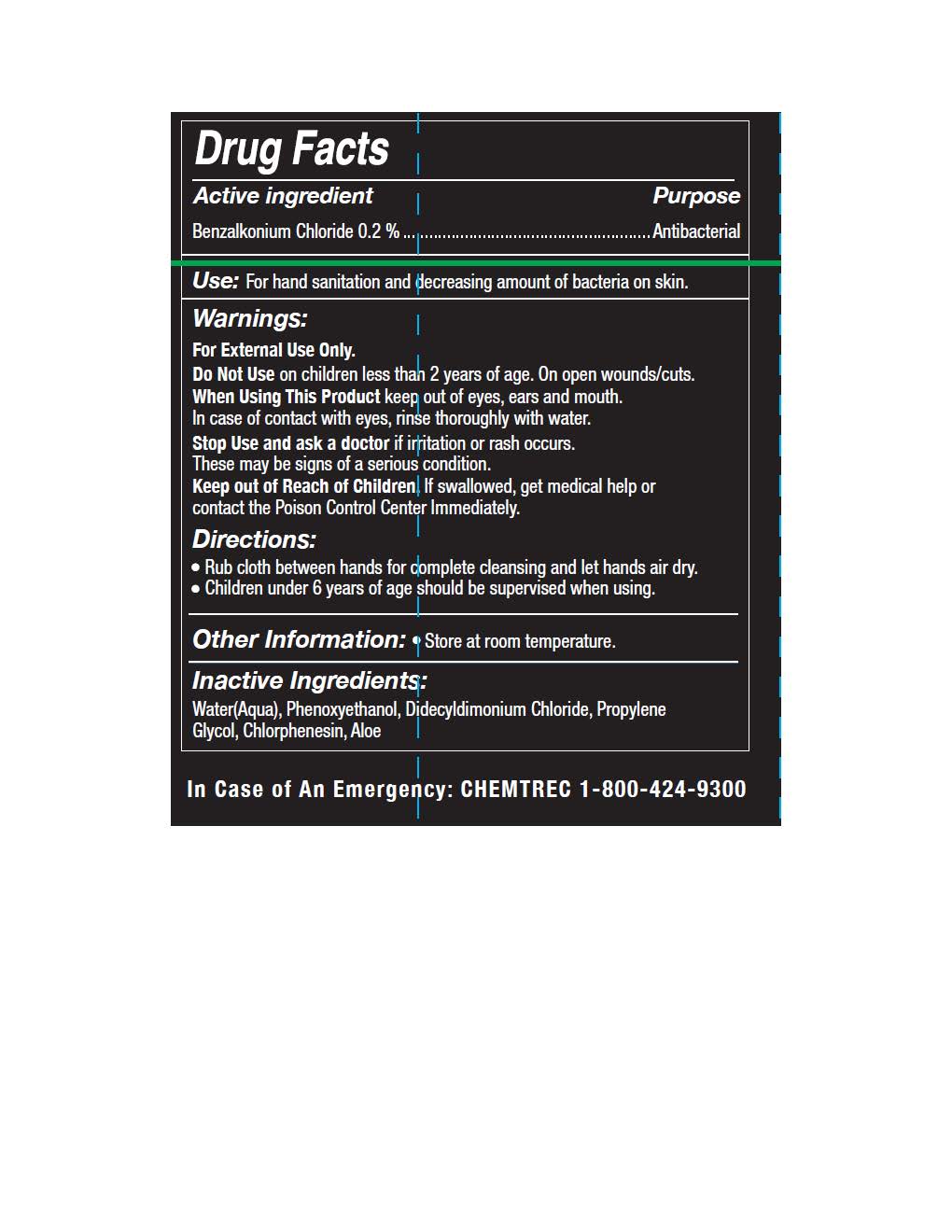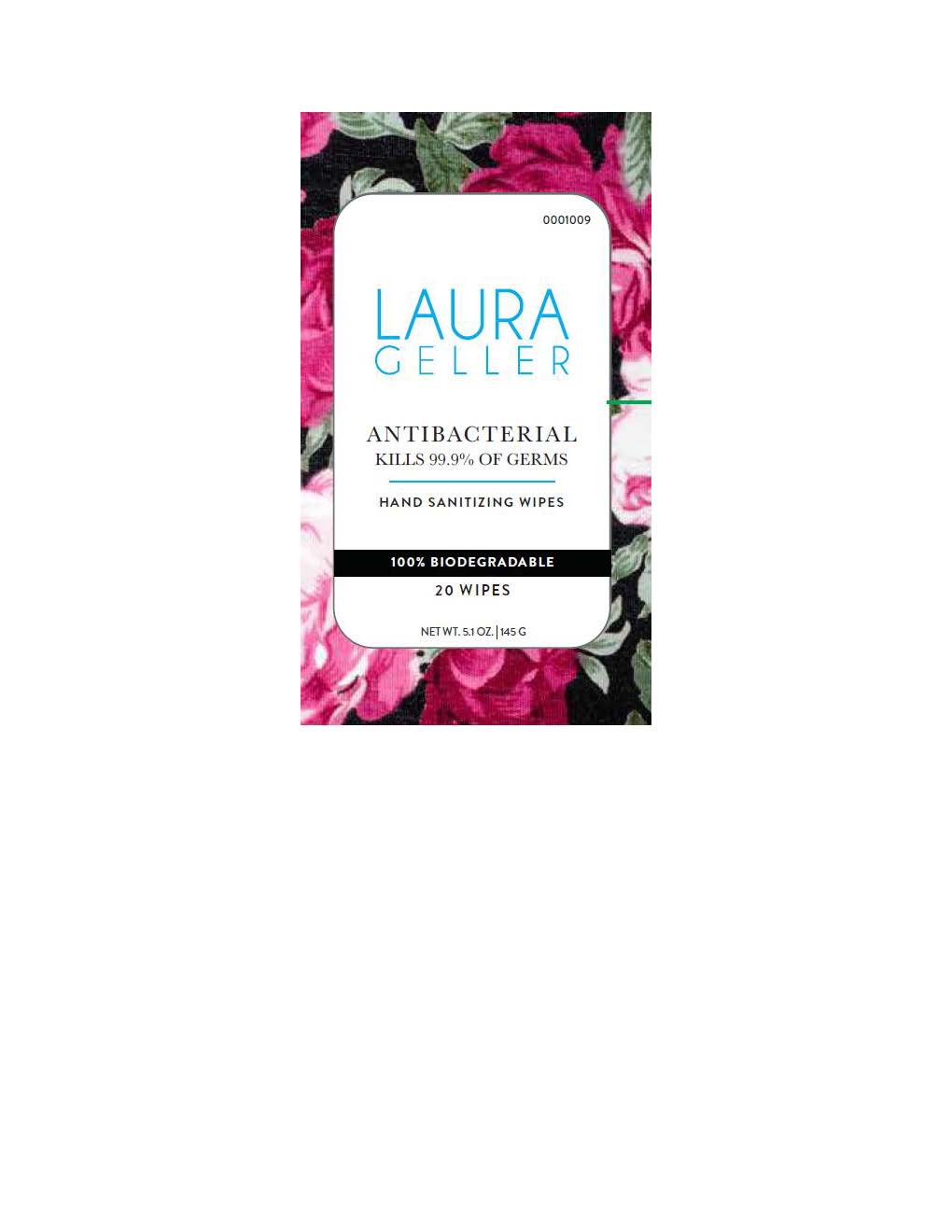 DRUG LABEL: Antibacterial Hand Wipes
NDC: 74884-220 | Form: CLOTH
Manufacturer: AS Beauty
Category: otc | Type: HUMAN OTC DRUG LABEL
Date: 20200605

ACTIVE INGREDIENTS: BENZALKONIUM CHLORIDE 0.2 g/0.2 g
INACTIVE INGREDIENTS: CHLORPHENESIN; DIDECYLDIMONIUM CHLORIDE; WATER; PROPYLENE GLYCOL; PHENOXYETHANOL

Usage

Rub Cloth Between Hands and let Air Dry

Non Active Ingredients

Water, Phenoxyethanol, Didecylmdimonium Chloride, Propylene Glycol, Chlophenesin

Usage indications

Stop uisng if irritation or rash occurs

Keep out of reach of Children

Benzalkonium Chloride

Antibacterial

Warnings

For External Use Only

Do no use on wounds or cuts

Keep out of contact of eyes, ears and mouth